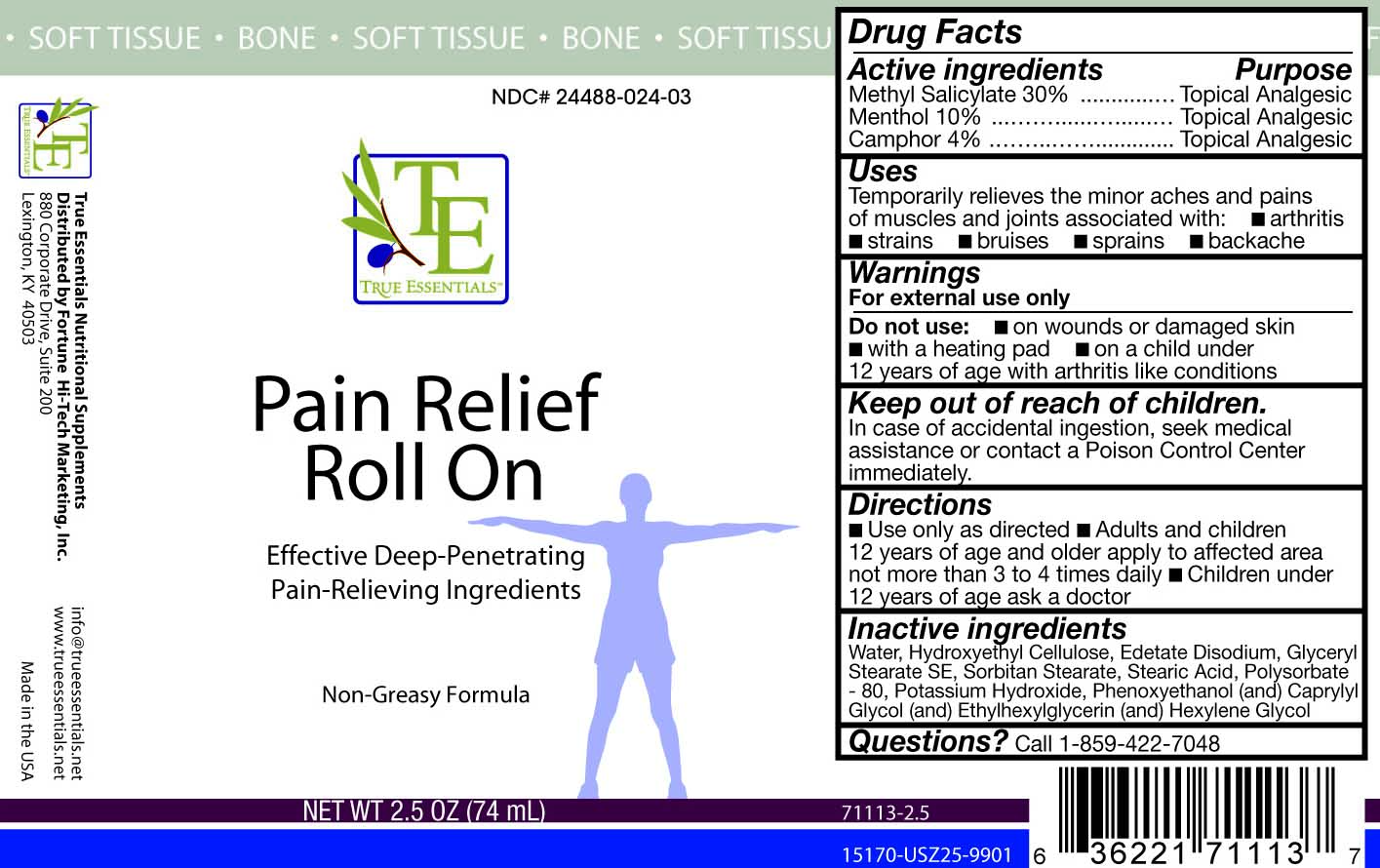 DRUG LABEL: True Essentials
NDC: 24488-024 | Form: GEL
Manufacturer: Fortune Hi-Tech Marketing, Inc
Category: otc | Type: HUMAN OTC DRUG LABEL
Date: 20100310

ACTIVE INGREDIENTS: CAMPHOR (SYNTHETIC) 2.96 mL/74 mL; Menthol 7.4 mL/74 mL; Methyl Salicylate 22.2 mL/74 mL
INACTIVE INGREDIENTS: Water; HYDROXYETHYL CELLULOSE (4000 MPA.S FOR 1% AQUEOUS SOLUTION); Edetate Disodium; Glyceryl Monostearate ; SORBITAN MONOSTEARATE; Polysorbate 80; Stearic Acid; Potassium Hydroxide; PHENOXYETHANOL; CAPRYLYL GLYCOL; ETHYLHEXYLGLYCERIN; HEXYLENE GLYCOL

Drug Facts

Active Ingredients

Camphor 4%
Menthol 10%
Methyl Salicylate 30%

Purpose

.……..…….............….. Topical Analgesic

...……......……….....… Topical Analgesic

.......….......… Topical Analgesic

Uses

Temporarily relieves the minor aches and pains of muscles and joints associated with:

- arthritis
- strains
- bruises
- sprains
- backache

Warnings

For external use only.

Do not use:

- on wounds or damaged skin
- with a heating pad
- on a child under 12 years of age with arthritis like conditions

Keep out of reach of children

In case of accidental ingestion, seek medical assistance or contact a Poison Control Center immediately.

Directions

■ Use only as directed
■ Adults and children 12 years of age and older apply
to affected area not more than 3 to 4 times daily
■ Children under 12 years of age ask a doctor

INACTIVE INGREDIENT

Water, Hydroxyethyl Cellulose, Edetate Disodium, Glyceryl Stearate Se, Sorbitan Stearate, Stearic Acid, Polysorbate 80, Potassium Hydroxide, Phenoxyethanol (and) Caprylyl Glycol (and) Ethylhexylglycerin (and) Hexylene Glycol

Questions?

Call 1-859-422-7048

PACKAGE LABEL

Placeholder Text